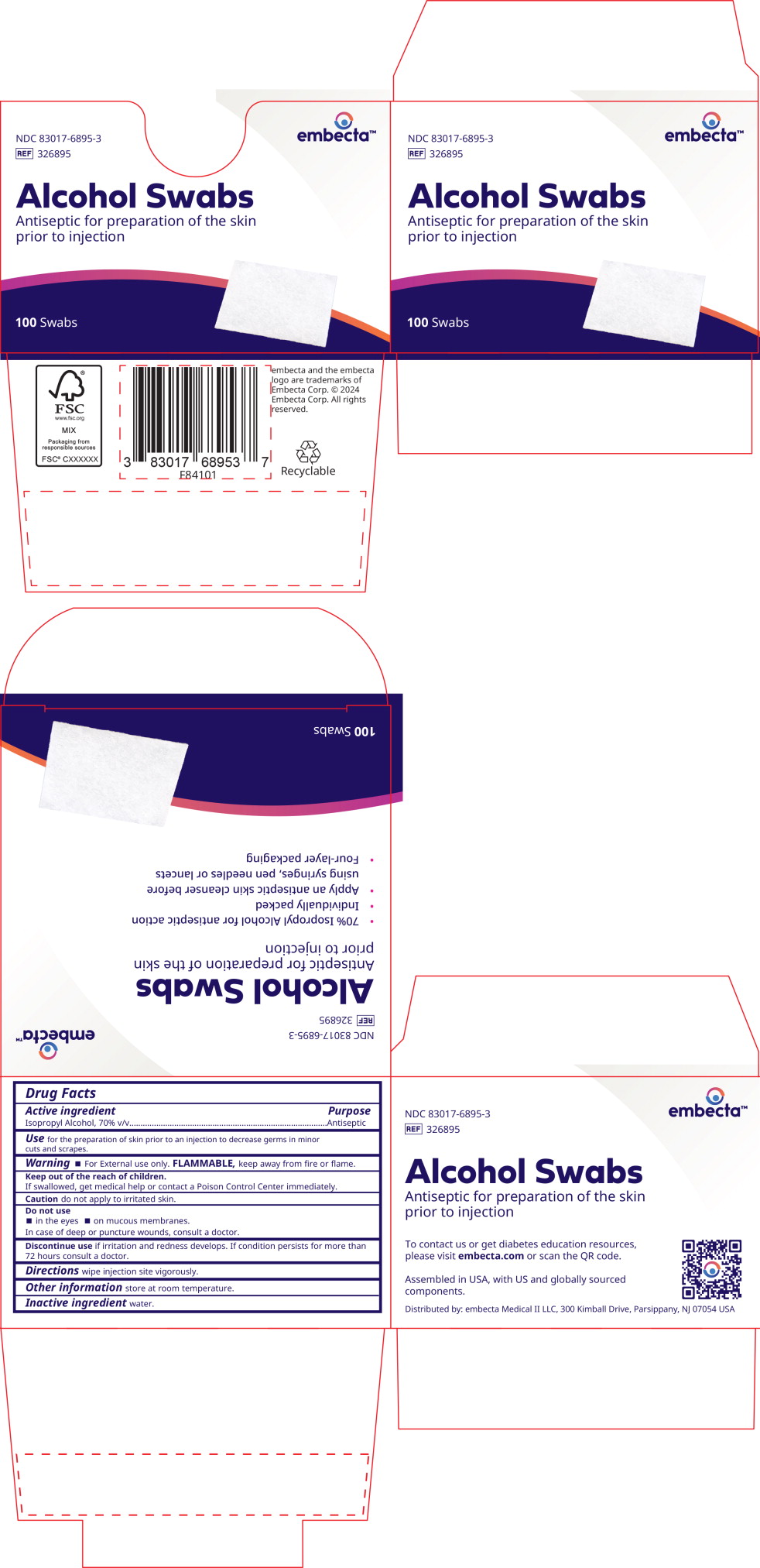 DRUG LABEL: Isopropyl Alcohol
NDC: 83017-6895 | Form: SWAB
Manufacturer: embecta Medical II, LLC
Category: otc | Type: HUMAN OTC DRUG LABEL
Date: 20240913

ACTIVE INGREDIENTS: Isopropyl Alcohol 0.75 g/1 1
INACTIVE INGREDIENTS: Water

Drug Facts

Active ingredient

Isopropyl Alcohol, 70% v/v

Purpose

Antiseptic

Use

for the preparation of skin prior to an injection to decrease germs in minor cuts and scrapes.

Warning

For External use only. FLAMMABLE, keep away from fire or flame.

Keep out of the reach of children.

If swallowed, get medical help or contact a Poison Control Center immediately.

Caution do not apply to irritated skin.

Do not use

- in the eyes
- on mucous membranes.

In case of deep or puncture wounds, consult a doctor.

Discontinue use if irritation and redness develops. If condition persists for more than 72 hours consult a doctor.

Directions

wipe injection site vigorously.

Other information

store at room temperature.

Inactive ingredient

water.

Principal Display Panel – 100 Swabs Carton Label

embecta™

NDC 83017-6895-3

REF 326895

Alcohol Swabs

Antiseptic for preparation of the skin prior to injection

100 Swabs